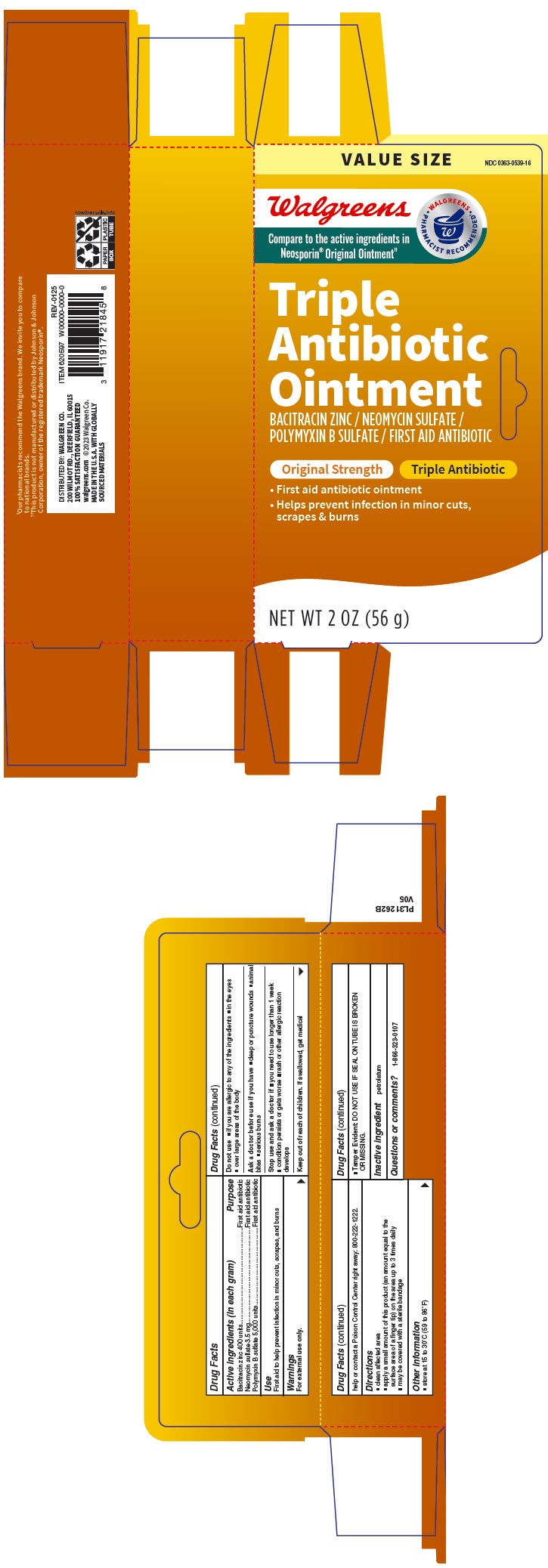 DRUG LABEL: triple antibiotic
NDC: 0363-0539 | Form: OINTMENT
Manufacturer: Walgreen Company
Category: otc | Type: HUMAN OTC DRUG LABEL
Date: 20250228

ACTIVE INGREDIENTS: BACITRACIN ZINC 400 [USP'U]/1 g; NEOMYCIN SULFATE 3.5 mg/1 g; POLYMYXIN B SULFATE 5000 [USP'U]/1 g
INACTIVE INGREDIENTS: PETROLATUM

Walgreen Co. Triple Antibiotic Ointment Drug Facts

Drug Facts

ACTIVE INGREDIENT

Active ingredients (in each gram) | Purpose
Bacitracin zinc 400 units | First aid antibiotic
Neomycin sulfate 3.5 mg | First aid antibiotic
Polymyxin B sulfate 5,000 units | First aid antibiotic

Use

First aid to help prevent infection in minor cuts, scrapes, and burns

Warnings

For external use only.

Do not use

- if you are allergic to any of the ingredients
- in the eyes
- over large areas of the body

Ask a doctor before use if you have

- deep or puncture wounds
- animal bites
- serious burns

Stop use and ask a doctor if

- you need to use longer than 1 week
- condition persists or gets worse
- rash or other allergic reaction develops

Keep out of reach of children. If swallowed, get medical help or contact a Poison Control Center right away: 800-222-1222.

Directions

- clean affected area
- apply a small amount of this product (an amount equal to the surface area of a finger tip) on the area up to 3 times daily
- may be covered with a sterile bandage

Other information

- store at 15 to 30°C (59 to 86°F)
- Tamper Evident: DO NOT USE IF SEAL ON TUBE IS BROKEN OR MISSING.

Inactive ingredient

petrolatum

Questions or comments?

1-866-323-0107

DISTRIBUTED BY: WALGREEN CO.
200 WILMOT RD., DEERFIELD, IL 60015

PRINCIPAL DISPLAY PANEL - 56 g Tube Carton

VALUE SIZE
NDC 0363-0539-16

Walgreens
Compare to the active ingredients in
Neosporin® Original Ointment††

WALGREENS
• PHARMACIST RECOMMENDED† •

Triple
Antibiotic
Ointment
BACITRACIN ZINC / NEOMYCIN SULFATE /
POLYMYXIN B SULFATE / FIRST AID ANTIBIOTIC

Original Strength
Triple Antibiotic

- First aid antibiotic ointment
- Helps prevent infection in minor cuts,
  scrapes & burns

NET WT 2 OZ (56 g)